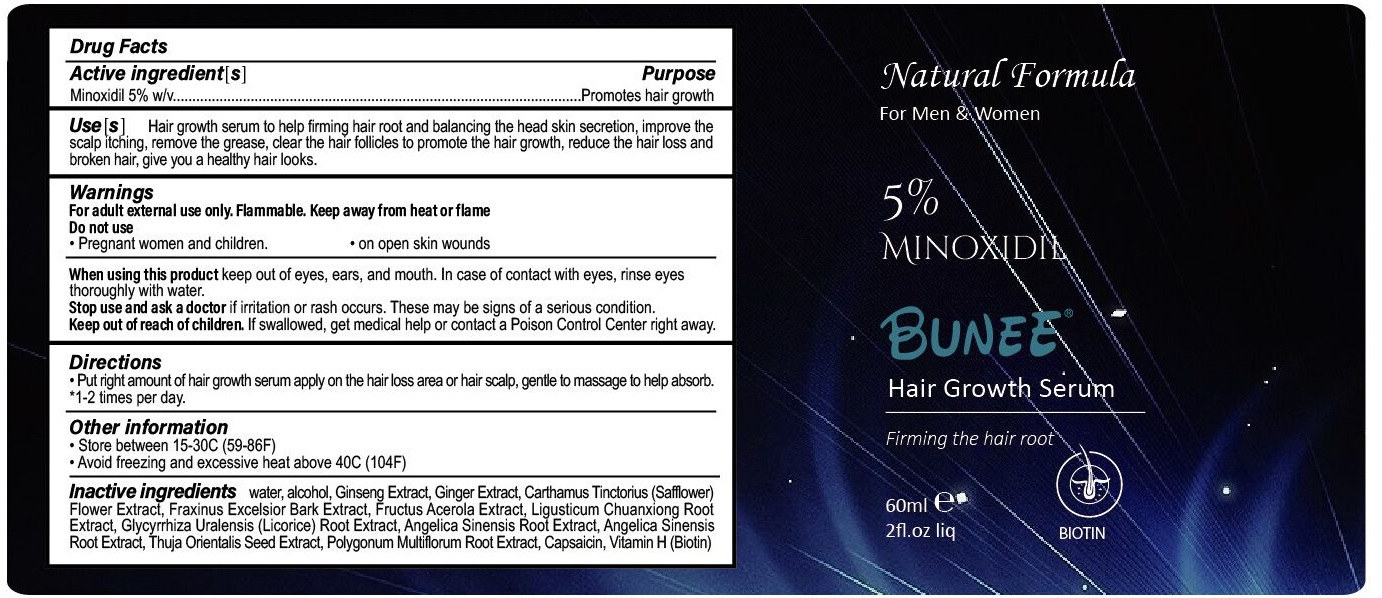 DRUG LABEL: BUNEE Hair Growth Serum
NDC: 81653-001 | Form: LIQUID
Manufacturer: Guangzhou Jianyuan Biological Technology Co., Ltd.
Category: otc | Type: HUMAN OTC DRUG LABEL
Date: 20250116

ACTIVE INGREDIENTS: MINOXIDIL 5 g/100 mL
INACTIVE INGREDIENTS: CAPSAICIN; PLATYCLADUS ORIENTALIS SEED; WATER; ALCOHOL; GINGER; LIGUSTICUM SINENSE SUBSP. CHUANXIONG ROOT; GLYCYRRHIZA URALENSIS ROOT; REYNOUTRIA MULTIFLORA ROOT; FRAXINUS EXCELSIOR BARK; ARCTIUM LAPPA WHOLE; ANGELICA SINENSIS ROOT; BIOTIN; ASIAN GINSENG; SAFFLOWER

81653-001 Update

ACTIVE INGREDIENT

Minoxidil

Keep out of reach of children.lf swallowed, get medical help or contact a Poison Control Center right away.

When using this product keep out of eyes, ears, and mouth. In case of contact with eyes, rinse eyes thoroughly with water.

Stop use and ask a doctor if irritation or rash occurs. These may be signs of a serious condition.

PURPOSE

Promotes hair growth

INACTIVE INGREDIENT

water, alcohol, Ginseng Extract, Ginger Extract, CARTHAMUS TINCTORIUS (SAFFLOWER) FLOWER EXTRACT， FRAXINUS EXCELSIOR BARK EXTRACT, FRUCTUS ACEROLA EXTRACT, LIGUSTICUM CHUANXIONG ROOT EXTRACT, GLYCYRRHIZA URALENSIS (LICORICE) ROOT EXTRACT, Arctium Lappa L., ANGELICA SINENSIS ROOT EXTRACT, THUJA ORIENTALIS SEED EXTRACT, POLYGONUM MULTIFLORUM ROOT EXTRACT, Capsaicin, Vitamin H (Biotin)

Use[s]

Hair growth serum to help firming hair root and balancing the head skin secretion, improve thescalp itching, remove the grease, clear the hair follicles to promote the hair growth, reduce the hair loss and broken hair, give you a healthy hair looks.

Directions

Put right amount of hair growth serum apply on the hairloss area or hair scalp, gentle to massage to help absort.

1-2 times per day.

Other information

Store between 15-30°C (59-86°F)
Avoid freezing and excessive heat above 40°C (104°F)

DO NOT USE

Pregnant women and children.
on open skin wounds

WARNINGS

For adult external use only. Flammable. Keep away from heat or flame